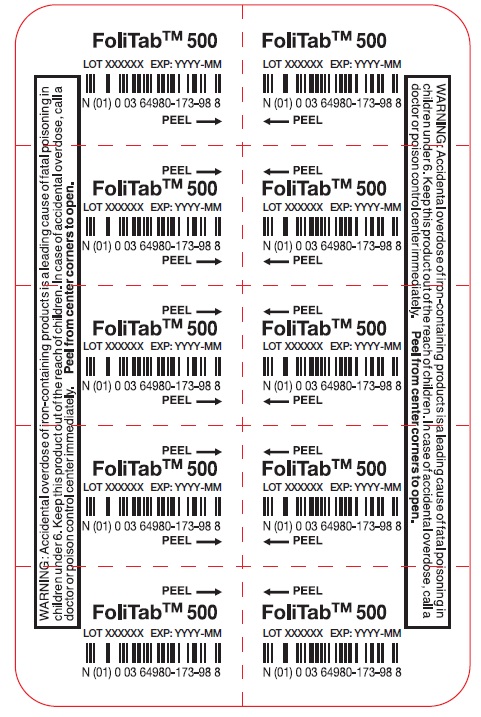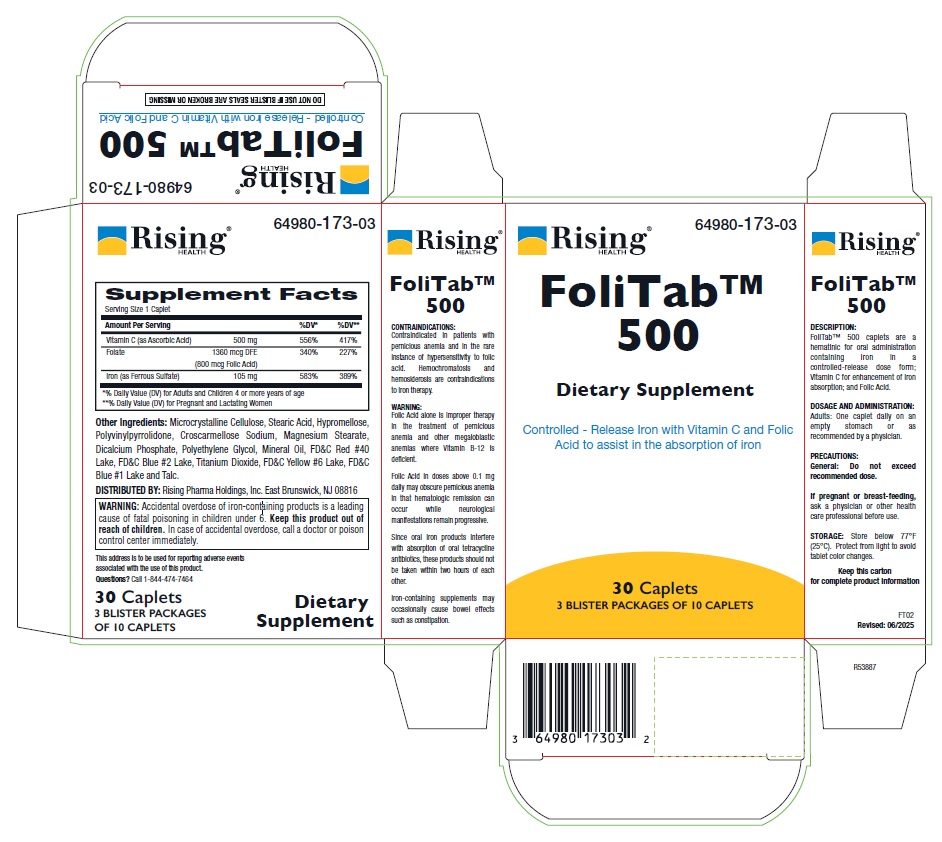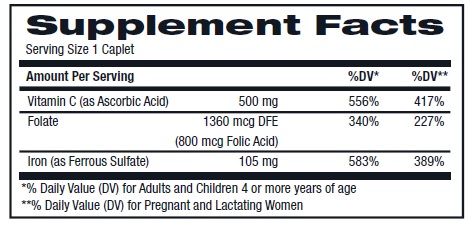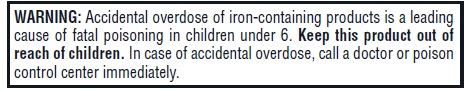 DRUG LABEL: FoliTab
NDC: 64980-173 | Form: TABLET
Manufacturer: Rising Pharma Holdings, Inc.
Category: other | Type: DIETARY SUPPLEMENT
Date: 20250621

ACTIVE INGREDIENTS: ASCORBIC ACID 500 mg/1 1; FOLIC ACID 1360 ug/1 1; IRON 105 mg/1 1
INACTIVE INGREDIENTS: Microcrystalline Cellulose; Stearic Acid; HYPROMELLOSE, UNSPECIFIED; COPOVIDONE K25-31; Croscarmellose Sodium; Magnesium Stearate; Dicalcium Phosphate; Polyethylene Glycol; Mineral Oil; FD&C RED NO. 40; FD&C BLUE NO. 2; Titanium Dioxide; FD&C YELLOW NO. 6; FD&C BLUE NO. 1; TALC

FoliTab 500, Dietary Supplement, 30 Caplets

HEALTH CLAIM

Other ingredients: Microcrystalline Cellulose, Stearic Acid, Hypromellose, Polyvinylpyrrolidone, Croscarmellose Sodium, Magnesium Stearate, Dicalcium Phosphate, Polyethylene Glycol, Mineral Oil, FD&C Red #40 Lake, FD&C Blue #2 Lake, Titanium Dioxide, FD&C Yellow #6 Lake, FD&C Blue #1 Lake and Talc.

WARNINGS

CONTRAINDICATIONS:
Contraindicated in patients with pernicious anemia and in the rare instance of hypersensitivity to folic acid. Hemochromatosis and hemosiderosis are contraindications to iron therapy.

WARNING:

Folic Acid alone is improper therapy in the treatment of pernicious anemia and other megaloblastic anemias where Vitamin B-12 is deficient.

Folic Acid in doses above 0.1 mg daily may obscure pernicious anemia in that hematologic remission can occur while neurological manifestations remain progressive.

Since oral iron products interfere with absorption of oral tetracycline antibiotics, these products should not be taken within two hours of each other.

Iron-containing supplements may occasionally cause bowel effects such as constipation.

DOSAGE AND ADMINISTRATION

DESCRIPTION:
FoliTab™ 500 caplets are a hematinic for oral administration containing iron in a controlled-release dose form; Vitamin C for enhancement of iron
absorption; and Folic Acid.

DOSAGE AND ADMINISTRATION:
Adults: One caplet daily on an empty stomach or as recommended by a physician.

PRECAUTIONS:

General: Do not exceed recommended dose.

If pregnant or breast-feeding, ask a physician or other health care professional before use.

STORAGE:

Store below 77°F (25°C). Protect from light to avoid tablet color changes.

Keep this carton for complete product information.

DISTRIBUTED BY: Rising Pharma Holdings, Inc. East Brunswick, NJ 08816

This address is to be used for reporting adverse events associated with the use of this product.

Questions? Call 1-844-474-7464

FT02

Revised: 06/2025

PACKAGE LABEL.PRINCIPAL DISPLAY PANEL

FoliTab 500

Dietary Supplement

30 Caplets

Bottle Label (64980-173-03)

FoliTab 500

Dietary Supplement

3 Blister Packages of 10 Caplets

Blsiter Label (64980-173-98)